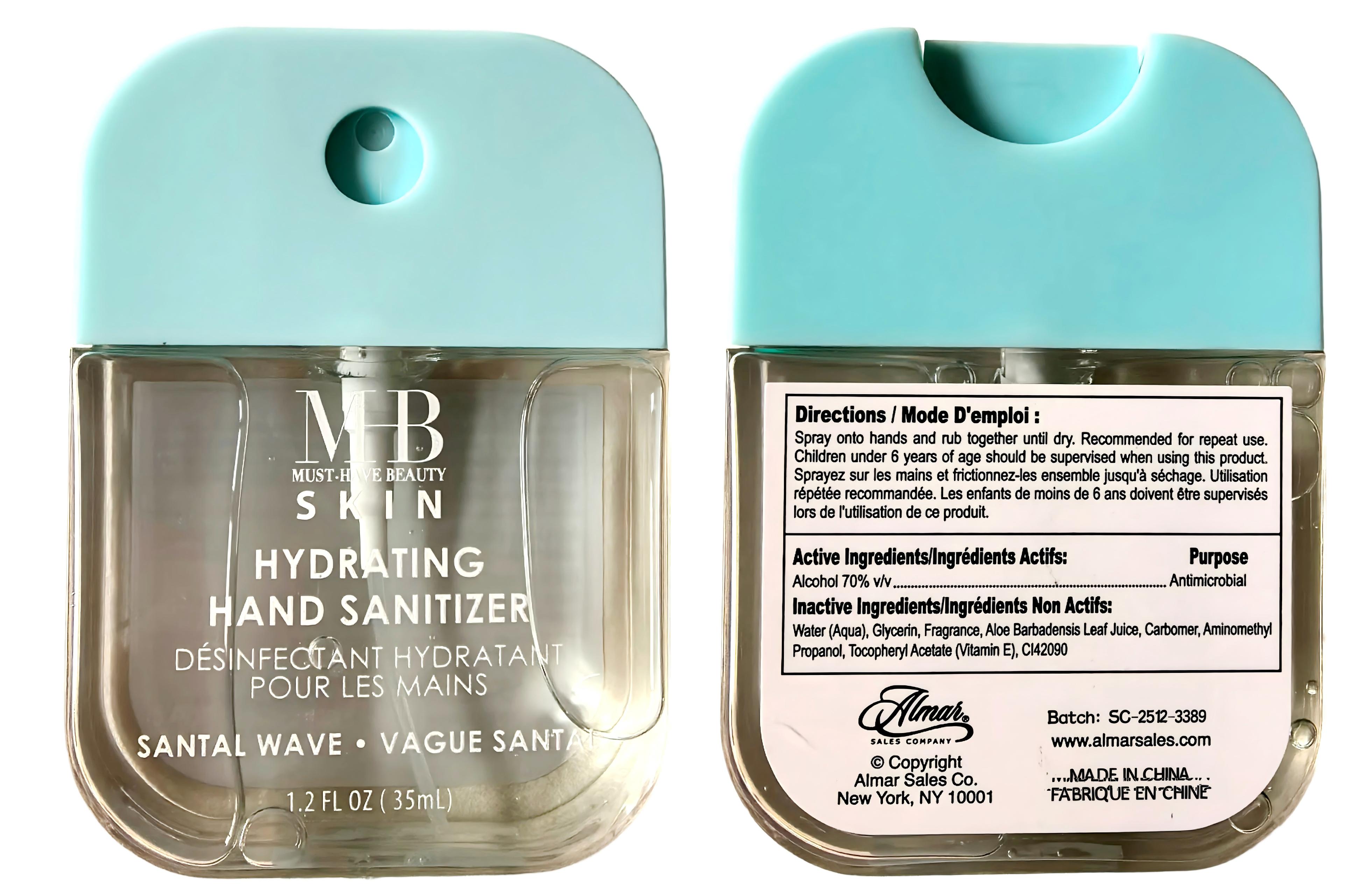 DRUG LABEL: MHB SKIN HYDRATING HAND SANITIZER SANTAL WAVE 35ml
NDC: 75328-211 | Form: SPRAY
Manufacturer: CROWN (YANGZHOU) HEALTH & BEAUTY CO., LTD.
Category: otc | Type: HUMAN OTC DRUG LABEL
Date: 20260125

ACTIVE INGREDIENTS: ALCOHOL 70 mL/100 mL
INACTIVE INGREDIENTS: FRAGRANCE 13576; ALPHA-TOCOPHEROL ACETATE; AMINOMETHYLPROPANOL; AQUA; ALOE BARBADENSIS LEAF JUICE; CI 42090; GLYCERIN; CARBOMER

Directions:

Spray onto hands and rub together until dry. Recommended for repeat use.Children under 6 years of age should be supervised when using this product.

Inactive Ingredients：

Water (Aqua), Glycerin, Fragrance, Aloe Barbadensis Leaf Juice, Carbomer, Aminomethyl Propanol, Tocopheryl Acetate (Vitamin E). CI42090

Warnings：

For external use only, Flammable, keep away from fire or flame.

When using this product:

In case of contact with eyes, rinse eyes thoroughly with water. Avoid contact with broken skin

Stop use and ask a doctor if:

lrritation and redness occurs

Keep out of reach of children:

If swallowed, get medical help or contact a Poison Control Center.

Active Ingredients:

Ethyl Alcohol 70% v/v Purpose: Antimicrobial

Use:

Hand sanitizer helps reduce bacteria and the spread of germs.